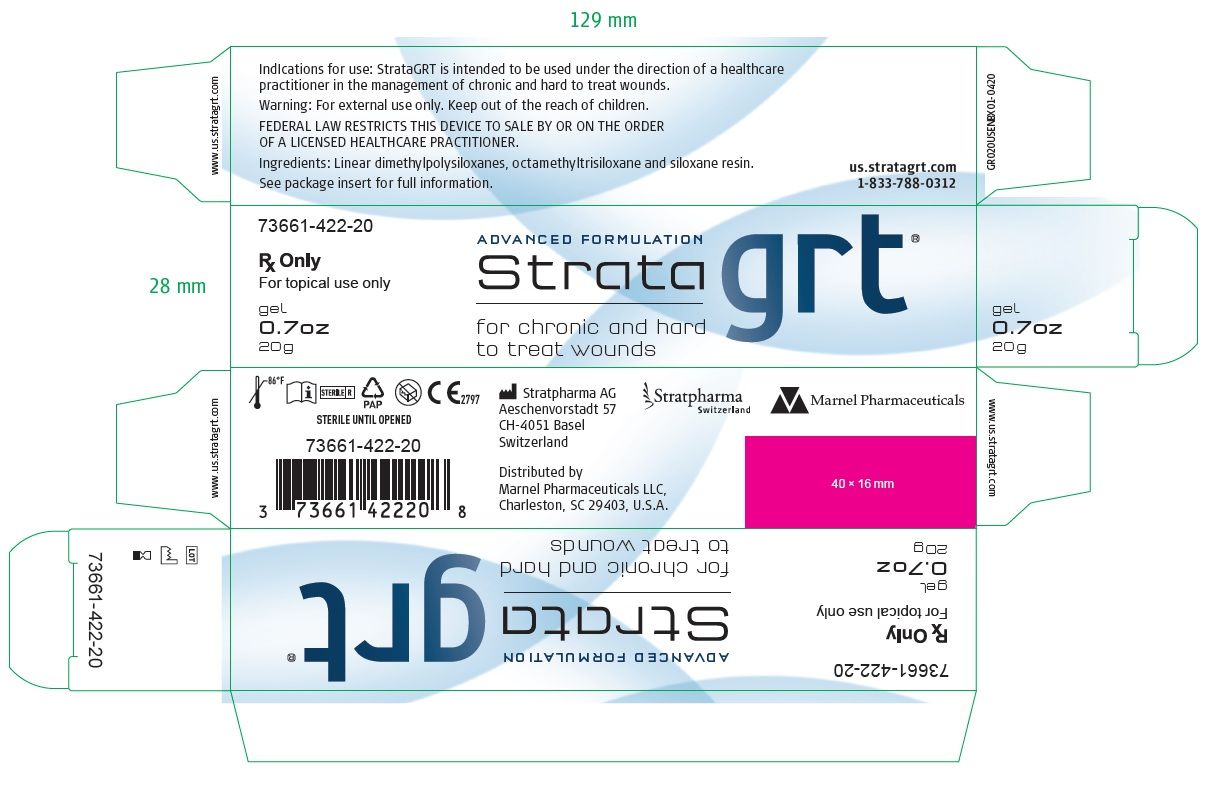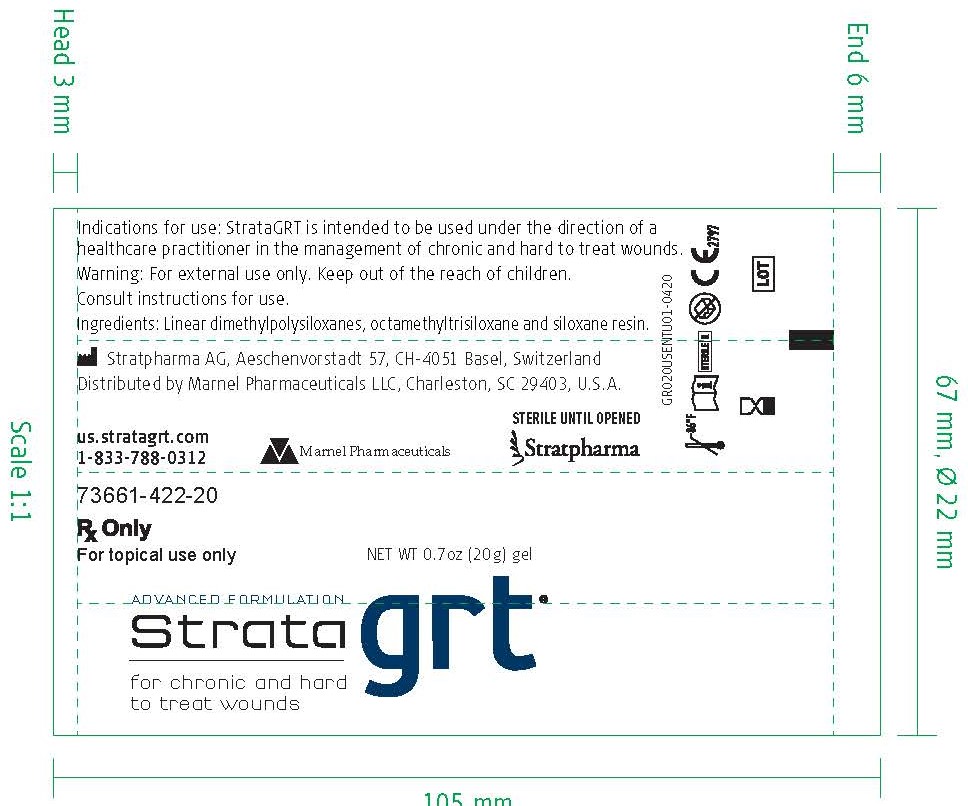 DRUG LABEL: StrataGRT
NDC: 73661-422
Manufacturer: Marnel Pharmaceuticals, Inc.
Category: other | Type: MEDICAL DEVICE
Date: 20200711
INACTIVE INGREDIENTS: DIMETHICONE; TRISILOXANE; TRIMETHYLSILOXYSILICATE (M/Q 0.6-0.8)

StrataGRT

WARNINGS AND PRECAUTIONS

Rx Only

For topical use only

Federal Law restricts this device to sale by or on the order of a licensed healthcare practitioner.

[EN] Description

StrataGRT is an occlusive, non-resorbable, self-drying and transparent gel.

When used as directed, StrataGRT dries to form a protective layer that is gas permeable and waterproof which hydrates and protects chronic and hard to treat wounds.

StrataGRT helps to promote a moist healing environment. This moist wound healing environment promotes faster re-epithelialization* and reduces the skin's acute inflammatory response.

StrataGRT is suitable for exposed areas like the face and neck as well as joints and hairy areas without the need for shaving.

INDICATIONS AND USAGE

Indication for use

StrataGRT is intended to be used under the direction of healthcare practitioners in the management of chronic and hard to treat wounds.

StrataGRT is indicated for use on all types of chronic and acute wounds.

StrataGRT may be directly applied to fresh incisions and excisions, open wounds and compromised skin surfaces.

StrataGRT gel is bacteriostatic and inert.

StrataGRT contains no alcohols, parabens or fragrances.

StrataGRT can be used with or without a secondary protective dressing.

StrataGRT is suitable for infants, children, people with sensitive skin, during pregnancy and while breastfeeding.

StrataGRT is intended for single patient use.

INDICATIONS AND USAGE

Directions for use

On first use of 0.7 oz (20 g) tubes remove the cap, cut the nozzle tip of the tube and close with the cap after use.

Ensure that the affected superficial area is cleaned before each application.

Gently pat dry as much excess exudate or wound fluid from the area as possible prior to gel application.

For best results StrataGRT should be maintained in continuous contact with the skin (24 hours a day/7 days aweek).

On wounds not requiring a secondary dressing:

Apply a thin layer of StrataGRT to the affected area and allow the gel to dry.

When applied correctly to exposed areas, StrataGRT should be dry in 5-6 minutes.

If it takes longer to dry you have probably applied too much.

Gently remove the excess with a clean tissue or gauze and allow the drying process to continue.

StrataGRT should be applied twice daily to exposed areas or as advised by your physician.

If StrataGRT has been removed by washing, it should be reapplied.

On wounds requiring a secondary dressing:

Apply a thin layer of StrataGRT then cover with secondary dressing.

Drying is not necessary.

StrataGRT should be reapplied when changing the dressing or checking the wound progress, or as advised by your physician.

PATIENT COUNSELING INFORMATION

How much StrataGRT do I need?

StrataGRT gel is an advanced formulation that requires substantially less product per application than creams or gels.

StrataGRT 0.7 oz (20g) is enough to treat an area of 5X5 inch (12X12 cm) twice per day for 30 days.

Warning

- For external use only.
- StrataGRT should not be placed in contact with the eyes.
- StrataGRT should not be applied over other skin treatment without the advice of your physician.
- StrataGRT may stain clothing if not completely dry. If staining occurs, dry cleaning should be able to remove it without damaging the fabric.
- For correct storage please reclose the tube tightly with the cap.
- If irritation occurs, discontinue use and consult your physician.
- Keep out of the reach of children.
- Do not use after the expiration (EXP) date printed on the tube. The expiration (EXP) date does not change once the tube has been opened.
- Do not use if the tube is damaged.

Contraindications

Do not administer to patients with known hypersensitivity to the ingredients of this product.

PATIENT COUNSELING INFORMATION

STERILE UNTIL OPENED

Ingredients: Linear dimethylpolysiloxanes, octamethyltrisiloxane and siloxane resin.

How supplied:

StrataGRT 0.7 oz (20g) tube

Product Identification code:

73661-422-20